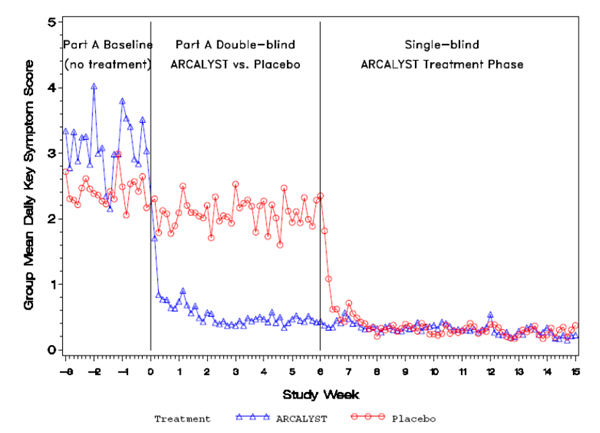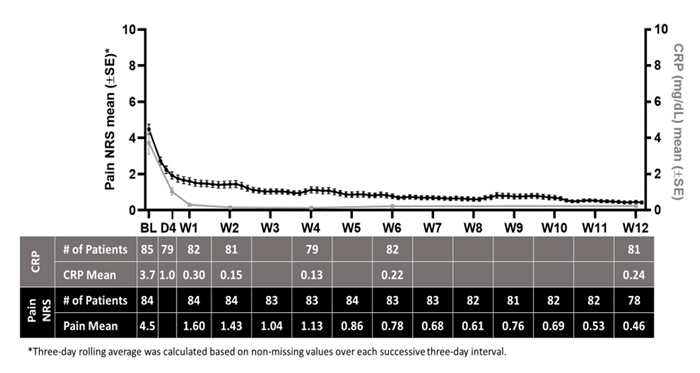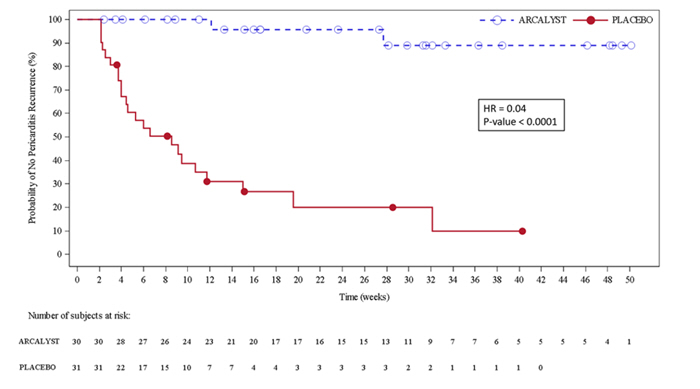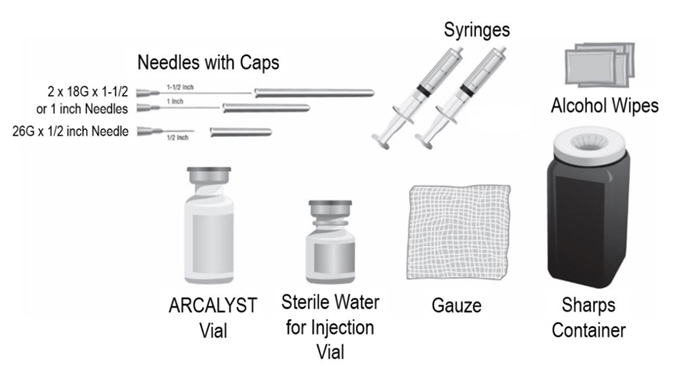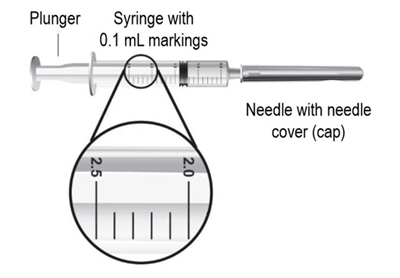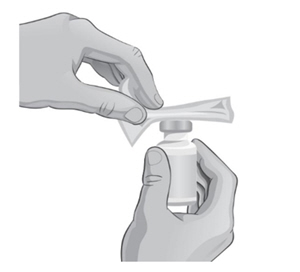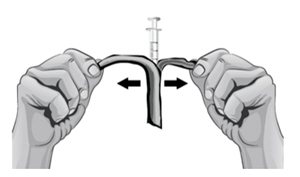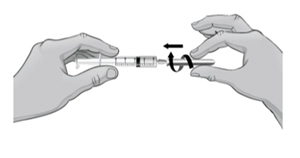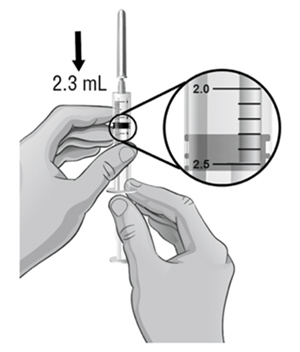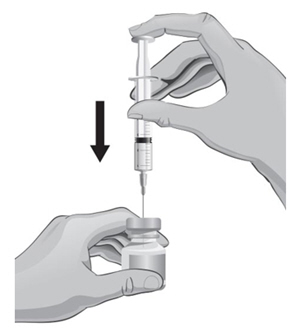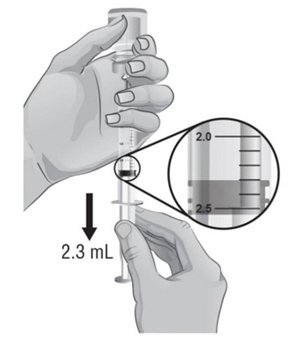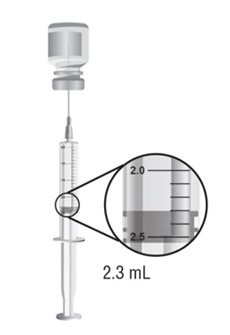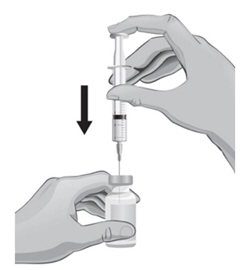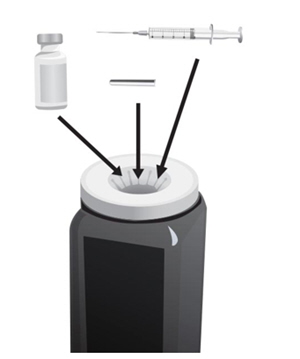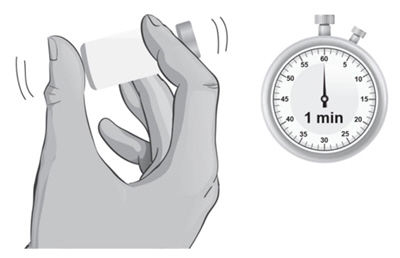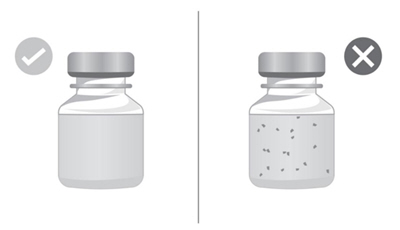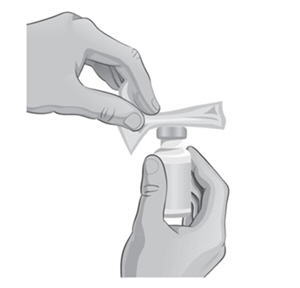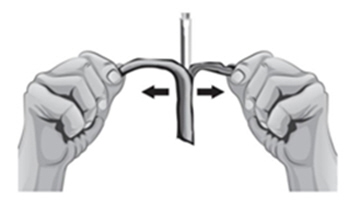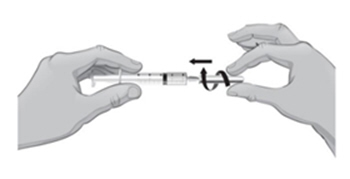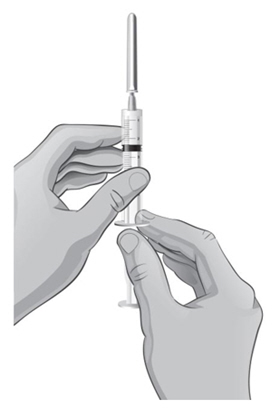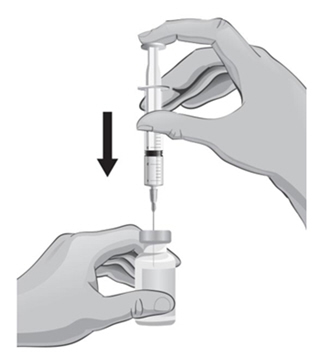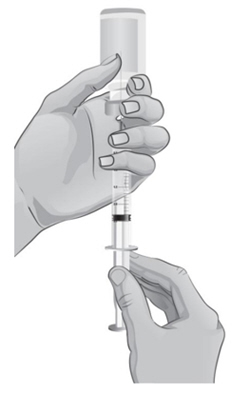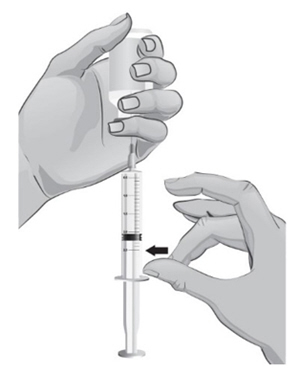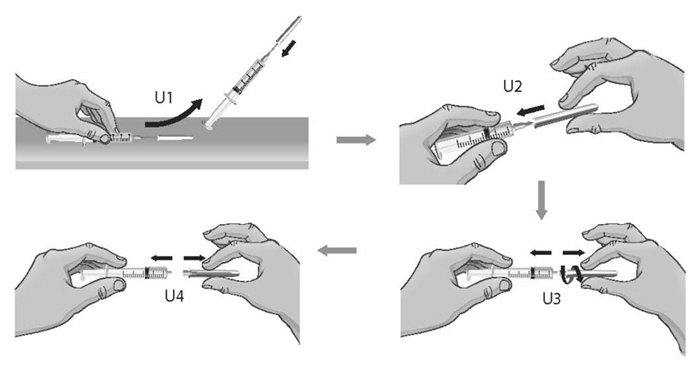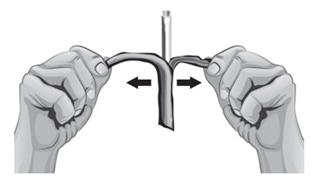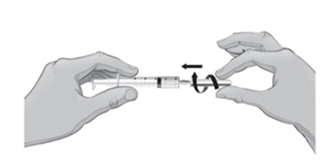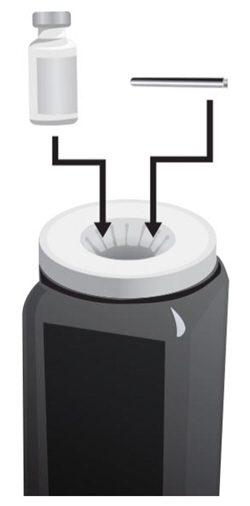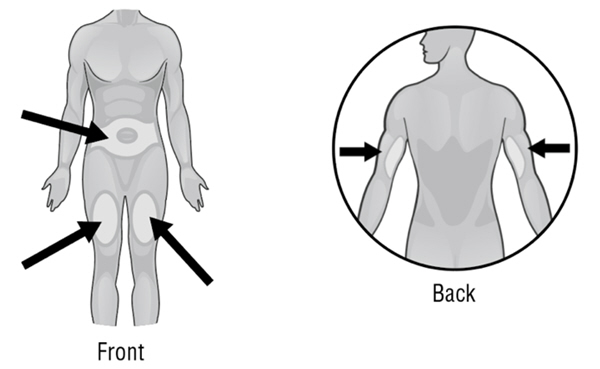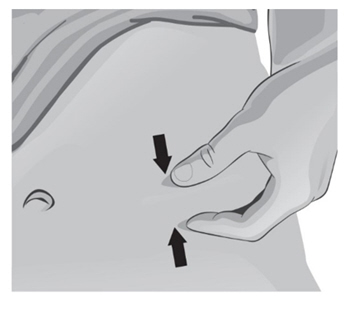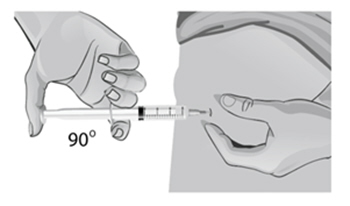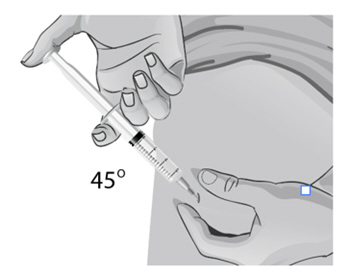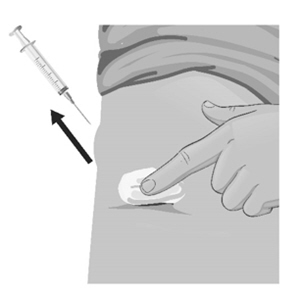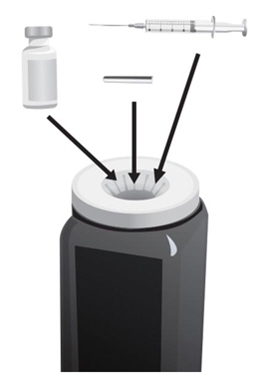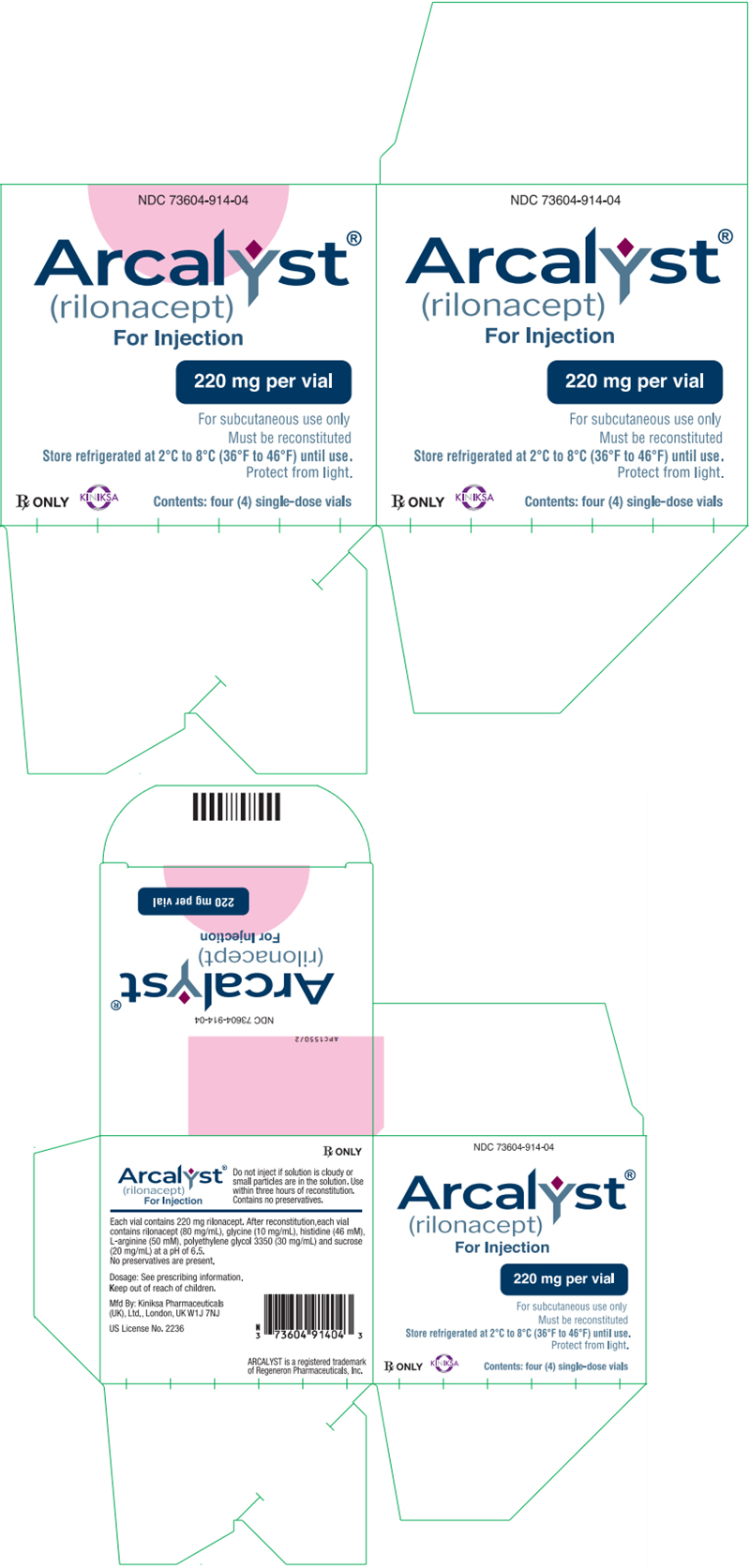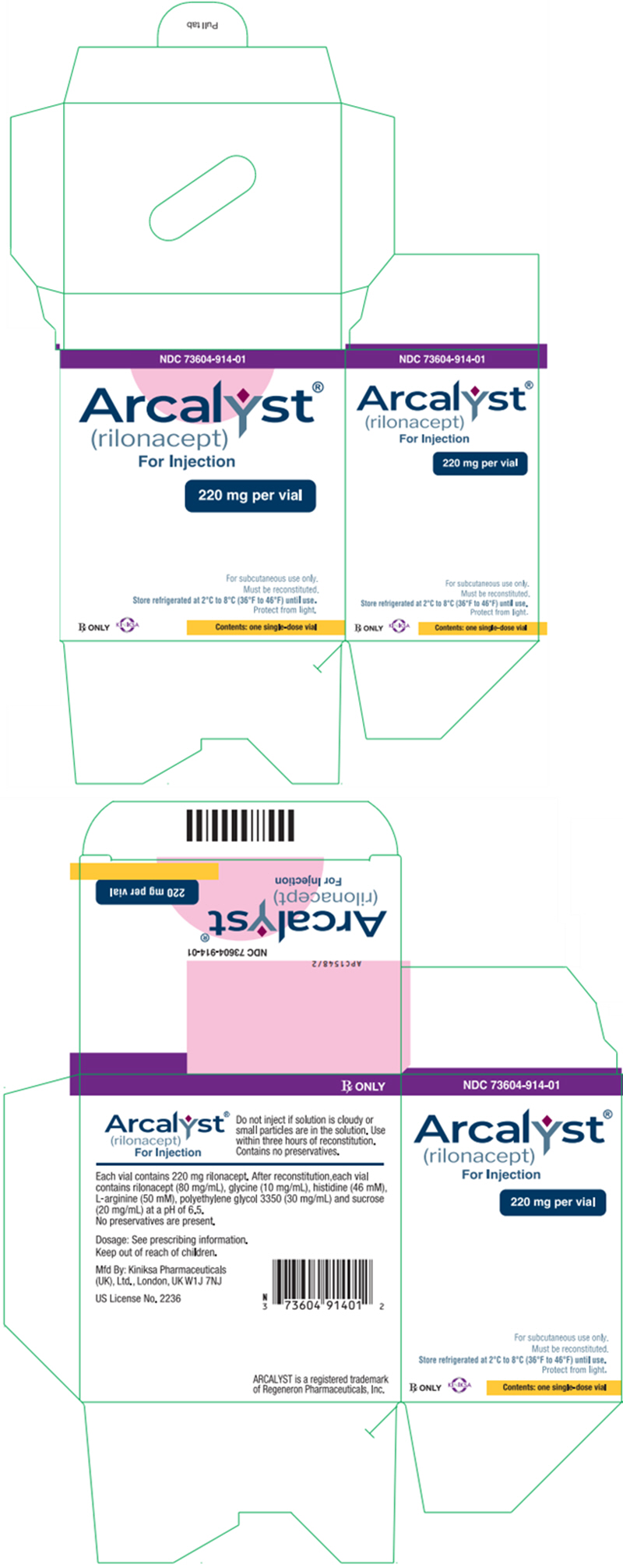 DRUG LABEL: Arcalyst
NDC: 73604-914 | Form: INJECTION, POWDER, LYOPHILIZED, FOR SOLUTION
Manufacturer: Kiniksa Pharmaceuticals (UK), Ltd.
Category: prescription | Type: HUMAN PRESCRIPTION DRUG LABEL
Date: 20251216

ACTIVE INGREDIENTS: RILONACEPT 160 mg/2 mL
INACTIVE INGREDIENTS: HISTIDINE; ARGININE; POLYETHYLENE GLYCOL 3350; SUCROSE; GLYCINE

HIGHLIGHTS OF PRESCRIBING INFORMATION

These highlights do not include all the information needed to use ARCALYST safely and effectively. See full prescribing information for ARCALYST.
ARCALYST® (rilonacept) for injection, for subcutaneous use
Initial U.S. Approval: 2008

RECENT MAJOR CHANGES

None.

1 INDICATIONS AND USAGE

ARCALYST (rilonacept) is an interleukin-1 blocker indicated for:

- Treatment of Cryopyrin-Associated Periodic Syndromes (CAPS), including Familial Cold Autoinflammatory Syndrome (FCAS), and Muckle-Wells Syndrome (MWS) in adults and children 12 years and older (1.1, 14.1)
- Maintenance of remission of Deficiency of Interleukin-1 Receptor Antagonist (DIRA) in adults and pediatric patients weighing 10 kg or more (1.2, 14.2)
- Treatment of recurrent pericarditis (RP) and reduction in risk of recurrence in adults and children 12 years and older (1.3, 14.3)

2 DOSAGE AND ADMINISTRATION

Administer by subcutaneous injection (2.1)

- CAPS, FCAS, MWS, and RP (2.2):
  Adults:
  - Loading dose: 320 mg, delivered as two 160 mg (2 mL) injections.
  - Maintenance dose: 160 mg (2 mL) injection once weekly.
  Pediatric patients 12 years to 17 years:
  - Loading dose: 4.4 mg/kg, up to a maximum of 320 mg, delivered as 1 or 2 injections (not to exceed 2 mL/injection).
  - Maintenance dose: 2.2 mg/kg, up to a maximum of 160 mg (2 mL) injection, once weekly.
- DIRA (2.3):
  Adults and pediatric patients weighing 10 kg or more:
  - 4.4 mg/kg up to a maximum of 320 mg, delivered as 1 or 2 injections (2 mL/injection) once weekly.

3 DOSAGE FORMS AND STRENGTHS

For injection: 220 mg of lyophilized powder in a single-dose vial for reconstitution. (3)

4 CONTRAINDICATIONS

None. (4)

5 WARNINGS AND PRECAUTIONS

- Serious Infections: Serious, life-threatening infections have been reported in patients taking ARCALYST. Do not initiate treatment with ARCALYST in patients with active or chronic infections. Discontinue treatment if a patient develops a serious infection. (5.1)
- Hypersensitivity Reactions: If a hypersensitivity reaction occurs, discontinue administration of ARCALYST and initiate appropriate therapy. (5.3)
- Immunizations: Avoid live vaccines. Update recommended vaccinations prior to initiation of therapy per current guidelines. (5.5)

6 ADVERSE REACTIONS

The most common adverse reactions reported by patients with CAPS and RP treated with ARCALYST are injection-site reactions and upper respiratory tract infections. (6.1)

To report SUSPECTED ADVERSE REACTIONS, contact Kiniksa at 1-833-KINIKSA (1-833-546-4572) or FDA at 1-800-FDA-1088 or www.fda.gov/medwatch.

8 USE IN SPECIFIC POPULATIONS

Pregnancy: Based on animal data, may cause fetal harm. (8.1)

FULL PRESCRIBING INFORMATION

1 INDICATIONS AND USAGE

1.1 Cryopyrin-Associated Periodic Syndromes, Familial Cold Autoinflammatory Syndrome and Muckle-Wells Syndrome

ARCALYST® (rilonacept) is an interleukin-1 blocker indicated for the treatment of Cryopyrin-Associated Periodic Syndromes (CAPS), including Familial Cold Autoinflammatory Syndrome (FCAS), and Muckle-Wells Syndrome (MWS) in adults and pediatric patients 12 years and older.

1.2 Deficiency of IL-1 Receptor Antagonist

ARCALYST is indicated for the maintenance of remission of Deficiency of Interleukin-1 Receptor Antagonist (DIRA) in adults and pediatric patients weighing at least 10 kg.

1.3 Recurrent Pericarditis

ARCALYST is indicated for the treatment of recurrent pericarditis (RP) and reduction in risk of recurrence in adults and pediatric patients 12 years and older.

2 DOSAGE AND ADMINISTRATION

2.1 General Dosing Information

ARCALYST is for subcutaneous use only.

2.2 Cryopyrin-Associated Periodic Syndromes, Familial Cold Autoinflammatory Syndrome, Muckle-Wells Syndrome and Recurrent Pericarditis

Adults: Initiate treatment with a loading dose of 320 mg delivered as two, 2-mL subcutaneous injections of 160 mg each, administered on the same day at two different injection sites. Continue dosing with a once-weekly injection of 160 mg administered as a single, 2-mL subcutaneous injection.

Pediatric patients 12 years to 17 years: Initiate treatment with a loading dose of 4.4 mg/kg, up to a maximum dose of 320 mg, administered as one or two subcutaneous injections, not to exceed single-injection volume of 2 mL per injection site. If the initial dose is given as two injections, administer on the same day at two different sites. Continue dosing with a once-weekly injection of 2.2 mg/kg, up to a maximum of 160 mg, administered as a single subcutaneous injection, up to 2 mL.

If a once-weekly dose is missed, instruct the patient to administer the injection within 7 days from the missed dose and then resume the patient's original schedule. If the missed dose is not administered within 7 days, instruct the patient to administer the dose, starting a new schedule based on this date.

2.3 Deficiency of IL-1 Receptor Antagonist

Adults: The recommended dose of ARCALYST is 320 mg, once weekly, administered as two subcutaneous injections on the same day at two different sites with a maximum single-injection volume of 2 mL. ARCALYST should not be given more often than once weekly.

Pediatric patients weighing 10 kg or more: The recommended dose of ARCALYST is 4.4 mg/kg (up to a maximum of 320 mg), once weekly, administered as one or two subcutaneous injections with a maximum single-injection volume of 2 mL. If the dose is given as two injections, administer both on the same day, each one at a different site.

When switching from another IL-1 blocker, discontinue the IL-1 blocker and begin ARCALYST treatment at the time of the next dose [see Drug Interactions (7.1)].

2.4 Preparation for Administration

Reconstitute each single-dose vial of ARCALYST with 2.3 mL of preservative-free Sterile Water for Injection, USP (supplied separately) prior to subcutaneous administration of the drug.

2.5 Administration

Using aseptic technique, withdraw 2.3 mL of preservative-free Sterile Water for Injection through an 18-gauge, 1- or 1½-inch needle attached to a 3-mL syringe and inject the preservative-free Sterile Water for Injection, USP, into the drug product vial for reconstitution. The needle and syringe used for reconstitution with preservative-free Sterile Water for Injection, USP, should then be discarded and should not be used for subcutaneous injections. After the addition of preservative-free Sterile Water for Injection, USP, reconstitute the vial contents by shaking the vial for approximately one minute and then allowing it to sit for one minute. The resulting 80mg/mL solution is sufficient to allow a withdrawal volume of up to 2 mL for subcutaneous administration. The reconstituted solution is viscous, clear, colorless to pale yellow, and free from particulates. Prior to injection, inspect the reconstituted solution for any discoloration or particulate matter. Discard the solution if either is observed.

Using aseptic technique, withdraw the recommended dose volume, up to 2 mL (160 mg), of the solution with a new 18-gauge, 1- or 1½-inch needle attached to a new 3-mL syringe. For the subcutaneous injection, replace the needle with a new 26-gauge, ½-inch needle. EACH VIAL SHOULD BE USED FOR A SINGLE DOSE ONLY. Discard the vial after withdrawal of drug.

After reconstitution, ARCALYST may be kept at room temperature, but keep it protected from light, and use the solution within three hours after reconstitution. Discard unused portions of ARCALYST.

Rotate the sites for subcutaneous injection, such as the abdomen, thigh, or upper arm. Injections should never be administered at sites that are bruised, red, tender, or hard.

3 DOSAGE FORMS AND STRENGTHS

For injection: 220 mg of rilonacept as a white to off-white lyophilized powder for reconstitution in single-dose vials.

4 CONTRAINDICATIONS

None.

5 WARNINGS AND PRECAUTIONS

5.1 Serious Infections

Interleukin-1 (IL-1) blockade may interfere with the immune response to infections. Treatment with another medication that works through inhibition of IL-1 has been associated with an increased risk of serious infections, and serious infections have been reported in patients taking ARCALYST [see Clinical Studies (14)]. There was a greater incidence of infections in CAPS and RP patients on ARCALYST compared with placebo.

In the controlled portion of the CAPS study [see Clinical Studies (14.1)], severe infection (bronchitis) was reported in one patient receiving ARCALYST. In an open-label extension study in CAPS, one patient developed bacterial meningitis and died [see Adverse Reactions (6.1)].

In clinical studies, ARCALYST has not been administered concomitantly with tumor necrosis factor (TNF) inhibitors. An increased incidence of serious infections has been associated with administration of an IL-1 blocker in combination with TNF inhibitors. ARCALYST is not recommended for use with TNF inhibitors because this may increase the risk of serious infections.

Drugs that affect the immune system by blocking TNF have been associated with an increased risk of reactivation of latent tuberculosis (TB). It is possible that taking drugs such as ARCALYST that block IL-1 increases the risk of TB or other atypical or opportunistic infections. Refer to current practice guidelines for evaluation and treatment of possible latent tuberculosis infections before initiating therapy with ARCALYST.

Treatment with ARCALYST should not be initiated in patients with an active or chronic infection. Discontinue ARCALYST if a patient develops a serious infection.

5.2 Risk of Malignancy

The impact of treatment with ARCALYST on the development of malignancies is not known. Treatment with immunosuppressants, including ARCALYST, may result in an increase in the risk of malignancies.

5.3 Hypersensitivity Reactions

Hypersensitivity reactions associated with ARCALYST occurred in clinical trials. If a hypersensitivity reaction occurs, discontinue ARCALYST and initiate appropriate therapy.

5.4 Lipid Profile Changes

Cholesterol and lipid levels may be reduced in patients with chronic inflammation. Increases in non-fasting lipid profile parameters occurred in patients treated with ARCALYST in clinical trials. Monitor patients' lipid profiles and consider lipid-lowering therapies if needed, based on cardiovascular risk factors and current guidelines [see Adverse Reactions (6.1)].

5.5 Immunizations

Since no data are available on the risks of secondary transmission of infection by live vaccines in patients receiving ARCALYST, avoid administration of live vaccines during treatment with ARCALYST.

No data are available on the effectiveness of vaccines in patients receiving ARCALYST. Since ARCALYST may interfere with normal immune response to new antigens, vaccines may not be effective in patients receiving ARCALYST.

Because IL-1 blockade may interfere with immune response to infections, it is recommended that prior to initiation of therapy with ARCALYST, adult and pediatric patients receive all recommended vaccinations, as per current immunization guidelines, including pneumococcal vaccine and inactivated influenza vaccine.

6 ADVERSE REACTIONS

The following clinically significant adverse reactions are described elsewhere in the labeling.

- Serious Infections [see Warnings and Precautions (5.1)]
- Risk of Malignancy[see Warnings and Precautions (5.2)]
- Hypersensitivity Reactions [see Warnings and Precautions (5.3)]
- Lipid Profile Changes [see Warnings and Precautions (5.4)]

6.1 Clinical Trial Experience

Clinical trials are conducted under widely varying conditions and, as such, adverse reaction rates observed cannot be directly compared to rates in the clinical trials of another drug and may not reflect the rates observed in clinical practice.

The data described herein reflect exposure to ARCALYST in over 2,000 patients who received at least one dose, including approximately 1700 exposed to 160 mg or more, of whom 151 patients were exposed for at least 6 months and 111 patients for at least one year. These included patients with CAPS and RP, patients with other diseases, and healthy volunteers.

CAPS

Approximately 60 patients with CAPS were treated weekly with 160 mg of ARCALYST. The pivotal trial population included 47 patients with CAPS. These patients were between the ages of 22 and 78 years (average 51 years). Thirty-one patients were female and 16 were male. All of the patients were White/Caucasian. Six pediatric patients (12 to17 years) were enrolled directly into the open-label extension phase of the trial.

Part A of the clinical trial was conducted in patients with CAPS who were naïve to treatment with ARCALYST. Part A of the study was a randomized, double-blind, placebo-controlled, six-week study comparing ARCALYST to placebo [see Clinical Studies (14)]. Table 1 reflects the frequency of adverse events reported by at least two patients during Part A.

Table 1: Most Frequent Adverse Reactions in Patients with CAPS (Part A, Reported by at Least Two Patients)
Adverse Event | ARCALYST 160 mg (n = 23) | Placebo (n= 24)
Any AE | 17 (74%) | 13 (54%)
Injection-site reactions | 11 (48%) | 3 (13%)
Upper respiratory tract infection | 6 (26%) | 1 (4%)
Nausea | 1 (4%) | 3 (13%)
Diarrhea | 1 (4%) | 3 (13%)
Sinusitis | 2 (9%) | 1 (4%)
Abdominal pain upper | 0 | 2 (8%)
Cough | 2 (9%) | 0
Hypoesthesia | 2 (9%) | 0
Stomach discomfort | 1 (4%) | 1 (4%)
Urinary tract infection | 1 (4%) | 1 (4%)

DIRA

In a 2-year, open-label study, 6 pediatric patients with DIRA, 3 years to 6 years of age, received a 2.2 to 4.4 mg/kg dose of ARCALYST once weekly [see Clinical Studies (14.2)]. The safety profile was generally consistent with that seen in patients with CAPS. The most common adverse reactions were upper respiratory infection (6 of 6), rash (5 of 6), otitis media (3 of 6), pharyngitis (3 of 6) and rhinorrhea (3 of 6).

RP

In the RP phase 3 study, a total of 86 patients received at least one dose of ARCALYST with a median treatment duration of 9 months [see Clinical Studies (14.3)]. Of the patients, 49 (57%) were female and 37 (43%) were male; 93% were White/Caucasian. The mean age was 44.7 years. Seven patients (8%) were aged 12-17 years old. No new adverse reactions were identified in this study.

Adverse Reactions of Special Interest

Injection-Site Reactions

In patients with CAPS or RP, the most common and consistently reported adverse event associated with ARCALYST was injection-site reaction (ISR). The ISRs included erythema, swelling, pruritus, mass, bruising, inflammation, pain, edema, dermatitis, discomfort, urticaria, vesicles, warmth and hemorrhage. Most injection-site reactions lasted for one to two days.

Infections

During Part A in the CAPS study, the incidence of patients reporting infections was greater with ARCALYST (48%) than with placebo (17%). In Part B, randomized withdrawal, the incidence of infections was similar in the ARCALYST (18%) and the placebo patients (22%). Part A of the trial was initiated in the winter months, while Part B was predominantly performed in the summer months.

In placebo-controlled studies across a variety of patient populations encompassing 360 patients treated with rilonacept and 179 treated with placebo, the incidence of infections was 34% and 27% (2.15 per patient-exposure year and 1.81 per patient-exposure year), respectively, for rilonacept and placebo.

Serious Infections

Six serious infections were reported by four patients during the CAPS clinical program: Mycobacterium intracellulare infection; gastrointestinal bleeding and colitis; sinusitis and bronchitis; and Streptococcus pneumoniae meningitis [see Adverse Reactions (6)].

One patient receiving ARCALYST for an unapproved indication in another study developed an infection in his olecranon bursa with Mycobacterium intracellulare. The patient was on chronic glucocorticoid treatment. The infection occurred after an intraarticular glucocorticoid injection into the bursa with subsequent local exposure to a suspected source of mycobacteria. The patient recovered after the administration of the appropriate antimicrobial therapy. One patient treated for another unapproved indication developed bronchitis/sinusitis, which resulted in hospitalization. One patient died in an open-label study of CAPS from Streptococcus pneumoniae meningitis.

Changes in Hematologic Parameters Laboratory Changes

One patient in a study in an unapproved indication developed transient neutropenia (ANC < 1 × 10^9/L) after receiving a large dose (2000 mg intravenously) of ARCALYST. The patient did not experience any infection associated with the neutropenia.

Lipid Profile Changes

Patients with CAPS treated with ARCALYST experienced increases in their mean total cholesterol, HDL cholesterol, LDL cholesterol, and triglycerides. The mean increases from baseline for total cholesterol, HDL cholesterol, LDL cholesterol, and triglycerides were 19 mg/dL, 2 mg/dL, 10 mg/dL, and 57 mg/dL, respectively, after 6 weeks of open-label therapy.

6.2 Immunogenicity

As with all therapeutic proteins, there is potential for immunogenicity. The detection of antibody formation is highly dependent on the sensitivity and specificity of the assay. The data reflect the percentage of patients whose test results were positive for antibodies to the rilonacept receptor domains in specific assays. Additionally, the observed incidence of antibody (including neutralizing antibody) positivity in an assay is highly dependent on several factors including assay sensitivity and specificity, assay methodology, sample handling, timing of sample collection, concomitant medications, and underlying disease. For these reasons, comparison of the incidence of antibodies to rilonacept with the incidence of antibodies in other studies or to other products may be misleading.

Antibodies directed against the receptor domains of rilonacept were detected by an ELISA assay in patients with CAPS after treatment with ARCALYST. Nineteen of 55 patients (35%) who had received ARCALYST for at least 6 weeks tested positive for treatment-emergent binding antibodies on at least one occasion. Of the 19, seven tested positive at the last assessment (Week 18 or 24 of the open-label extension period), and five patients tested positive for neutralizing antibodies on at least one occasion. There was no correlation of antibody activity and either clinical effectiveness or safety.

In the Phase 3 study of patients with RP, there were no patients who tested positive for antibodies at baseline. At any point in time, 26 out of 86 (30%) subjects tested positive at any assessment and of these, 6 tested positive for neutralizing antibodies (NAb). At the last assessment, 10 subjects remained positive for anti-drug antibodies (ADA) and 1 subject remained positive for NAb. There was no correlation of antibody activity and either clinical effectiveness or safety.

7 DRUG INTERACTIONS

7.1 TNF-Blocking Agent and IL-1 Blocking Agent

Specific drug interaction studies have not been conducted with ARCALYST. Concomitant administration of another drug that blocks IL-1 with a TNF-blocking agent in another patient population has been associated with an increased risk of serious infections and an increased risk of neutropenia. The concomitant administration of ARCALYST with TNF-blocking agents may also result in similar toxicities and is not recommended [see Warnings and Precautions (5.1)]. The concomitant administration of ARCALYST with other drugs that block IL-1 has not been studied. Based upon the potential for pharmacologic interactions between rilonacept and a recombinant IL-1ra, concomitant administration of ARCALYST and other agents that block IL-1 or its receptors is not recommended.

7.2 Cytochrome P450 Substrates

The formation of CYP450 enzymes is suppressed by increased levels of cytokines (e.g., IL-1) during chronic inflammation. Thus it is expected that for a molecule that binds to IL-1, such as rilonacept, the formation of CYP450 enzymes could be normalized. This is clinically relevant for CYP450 substrates with a narrow therapeutic index, where the dose is individually adjusted (e.g., warfarin). Upon initiation of ARCALYST in patients being treated with these types of medicinal products, therapeutic monitoring of the effect or drug concentration should be performed, and the individual dose of the medicinal product may need to be adjusted.

8 USE IN SPECIFIC POPULATIONS

8.1 Pregnancy

Risk Summary

Rare pregnancy outcomes reported postmarketing and from clinical trials, with very limited use of ARCALYST in pregnant women, are insufficient to evaluate for a drug-associated risk of major birth defects, miscarriage or adverse maternal or fetal outcomes. There may be risks to the mother and fetus associated with Cryopyrin Associated Periodic Syndromes (CAPS) (see Clinical Considerations). In an animal reproduction study, subcutaneous administration of rilonacept to pregnant monkeys during the period of organogenesis was complicated by losses of drug exposure as the study progressed, due to anti-drug antibody formation at all doses, but a dose-related increase in exposure was still evident. There were no treatment-related effects on fetal survival or development of malformations with doses up to 11 times the maximum recommended human dose (MRHD). Increased incidences of lumbar ribs, a skeletal variation, were observed in fetuses at doses approximately 2 times the MRHD and higher that slightly exceeded incidences in both control animals and the historical control database (see Data). There were findings of multiple fusion and absence of the ribs and thoracic vertebral bodies and arches in one fetus of the only pregnant monkey with exposure to rilonacept during the later period of gestation associated with a dose approximately 6 times the MRHD (see Data). The relationship of these findings in a single fetus to drug treatment was unclear, as these findings were not evident in fetuses from pregnant monkeys that had higher exposures to rilonacept during the period of organogenesis associated with a dose approximately 11 times the MRHD.

All pregnancies have a background risk of birth defect, loss, or other adverse outcomes. The estimated background risk of major birth defects and miscarriage for the indicated populations is unknown. In the U.S. general population, the estimated background risks of major birth defects and miscarriage in clinically recognized pregnancies is 2%–4% and of miscarriage is 15%–20%, respectively.

Clinical Considerations

Disease-Associated Maternal and/or Embryo/Fetal Risk

Published data suggest that increased maternal levels of interleukin (IL)-1β, which induces inflammation that occurs in CAPS, may be associated with pre-term birth.

Data

Animal Data

In an embryo-fetal development study, pregnant cynomolgus monkeys received rilonacept at subcutaneous doses of 0, 5, 15 or 30 mg/kg given twice a week from gestation days 20 to 48. The study was complicated by losses of drug exposure as the study progressed, due to anti-drug antibody formation at all doses, but a dose-related increase in exposure was still evident. There were no treatment-related effects on fetal survival or development of malformations with doses up to 11 times the MRHD (on a mg/kg basis with maternal subcutaneous doses up to 30 mg/kg). Increased incidences of lumbar ribs, a skeletal variation, were observed in fetuses at doses approximately 2 times the MRHD and higher (on a mg/kg basis with maternal subcutaneous doses of 5 mg/kg and higher) that slightly exceeded incidences in both control animals and the historical control database. There were findings of multiple fusion and absence of the ribs and thoracic vertebral bodies and arches in one fetus of the only pregnant monkey with exposure to rilonacept during the later period of gestation associated with a dose 6 times the MRHD (on a mg/kg basis with a maternal subcutaneous dose of 15 mg/kg). The relationship of these findings in a single fetus to drug treatment was unclear, as these findings were not evident in fetuses from pregnant monkeys that had higher exposures to rilonacept during the period of organogenesis associated with a dose approximately 11 times the MRHD (on a mg/kg basis with a maternal subcutaneous dose of 30 mg/kg). All doses of rilonacept reduced maternal serum levels of estradiol up to 64% compared to controls. In pre- and postnatal development studies in the mouse model using a murine analog of rilonacept (subcutaneous doses of 0, 20, 100 or 200 mg/kg), there was a small increase in the number of stillbirths in dams treated with 200 mg/kg three times per week.

8.2 Lactation

Risk Summary

There is no information on the presence of rilonacept in either human or animal milk, the effects on the breastfed infant, or the effects on milk production. The developmental and health benefits of breastfeeding should be considered along with the mother's clinical need for ARCALYST and any potential adverse effects on the breastfed child from ARCALYST or from the underlying maternal condition.

8.4 Pediatric Use

Cryopyrin-Associated Periodic Syndromes (CAPS) and Recurrent Pericarditis (RP)

Safety and effectiveness in pediatric patients with CAPS and RP below the age of 12 years have not been established.

Six pediatric patients with CAPS between the ages of 12 and 16 were treated with ARCALYST at a weekly subcutaneous dose of 2.2 mg/kg (up to a maximum of 160 mg) for 24 weeks during the open-label extension phase. These patients showed improvement from baseline in their symptom scores and in objective markers of inflammation (e.g., Serum Amyloid A and C-Reactive Protein). The adverse reactions included injection-site reactions and upper respiratory symptoms as were commonly seen in adult patients.

The trough drug levels for four pediatric patients measured at the end of the weekly dose interval (mean 20 mcg/mL, range 3.6 to 33 mcg/mL) were similar to those observed in adult patients with CAPS (mean 24 mcg/mL, range 7 to 56 mcg/mL).

In the Phase 3 study RHAPSODY, 7 patients aged 12 years to 17 years were treated with ARCALYST subcutaneously with an initial loading dose of 4.4 mg/kg (up to a maximum of 320 mg) followed by 2.2 mg/kg (up to a maximum of 160 mg) weekly. These patients were treated for a median time of 15 weeks. There were no apparent differences in efficacy, safety or tolerability across age groups.

When administered to pregnant primates, rilonacept treatment may have contributed to alterations in bone ossification in the fetus. It is not known if ARCALYST will alter bone development in pediatric patients. Pediatric patients treated with ARCALYST should undergo appropriate monitoring for growth and development. [see Use in Specific Populations (8.1)]

Deficiency of Interleukin-1 Receptor Antagonist (DIRA)

Safety and effectiveness in pediatric patients with DIRA weighing 10 kg or more have been established [see Adverse Reactions (6.1) and Clinical Studies (14.2)]. Safety and effectiveness of ARCALYST have not been established in pediatric patients weighing less than 10 kg for maintenance of remission of DIRA.

8.5 Geriatric Use

In the placebo-controlled clinical studies, 78 patients randomized to treatment with ARCALYST were ≥ 65 years of age, and 6 were ≥ 75 years of age. In the CAPS clinical trial, efficacy, safety and tolerability were generally similar in elderly patients as compared to younger adults; however, only ten patients ≥ 65 years old participated in the trial. In an open-label extension study of CAPS, a 71-year-old woman developed bacterial meningitis and died [see Adverse Reactions (6.1)]. Age did not appear to have a significant effect on steady-state trough concentrations in the clinical study.

8.6 Patients with Renal Impairment

No studies have been conducted to evaluate the pharmacokinetics of rilonacept administered subcutaneously in patients with renal impairment.

8.7 Patients with Hepatic Impairment

No studies have been conducted to evaluate the pharmacokinetics of rilonacept administered subcutaneously in patients with hepatic impairment.

10 OVERDOSAGE

There have been no reports of overdose with ARCALYST. Maximum weekly doses of up to 320 mg have been administered subcutaneously for up to approximately 18 months in a small number of patients with CAPS and up to 6 months in patients with an unapproved indication in clinical trials without evidence of dose-limiting toxicities. In addition, ARCALYST given intravenously at doses up to 2000 mg monthly in another patient population for up to six months was tolerated without dose-limiting toxicities. The maximum amount of ARCALYST that can be safely administered has not been determined.

In case of overdose, it is recommended that the patient be monitored for any signs or symptoms of adverse reactions or effects, and appropriate symptomatic treatment instituted immediately.

11 DESCRIPTION

Rilonacept is a dimeric fusion protein consisting of the ligand-binding domains of the extracellular portions of the human interleukin-1 receptor component (IL-1R1) and IL-1 receptor accessory protein (IL-1RAcP) linked in-line to the Fc portion of human IgG1. Rilonacept has a molecular weight of approximately 251 kDa. Rilonacept is expressed in recombinant Chinese hamster ovary (CHO) cells.

ARCALYST is supplied in single-dose vials containing a sterile, white to off-white lyophilized powder. Each vial of ARCALYST is to be reconstituted with 2.3 mL of Sterile Water for Injection, USP. A volume of up to 2 mL can be withdrawn, which is designed to deliver 160 mg for subcutaneous administration only. The resulting solution is viscous, clear, colorless to pale yellow, and essentially free from particulates. Each vial contains 220 mg rilonacept. After reconstitution, each vial contains rilonacept (80 mg/mL), glycine (10 mg/mL), histidine (46 mM), L-arginine (50 mM), polyethylene glycol 3350 (30 mg/mL), and sucrose (20 mg/mL) at a pH of 6.5. No preservatives are present.

12 CLINICAL PHARMACOLOGY

12.1 Mechanism of Action

Rilonacept is an interleukin-1 alpha (IL-1α) and interleukin-1 beta (IL-1β) cytokine trap. Rilonacept blocks IL-1 signaling by acting as a soluble decoy receptor that binds both IL-1α and IL-1β and prevents its interaction with cell surface receptors. Rilonacept also binds interleukin-1 receptor antagonist (IL-1ra). The equilibrium dissociation constants for rilonacept binding to IL-1α, IL-1β, and IL-1ra were 1.4 pM, 0.5 pM, and 6.1 pM, respectively.

CAPS refers to rare genetic syndromes generally caused by mutations in the NLRP-3 [nucleotide-binding domain, leucine rich family (NLR), pyrin domain containing 3] gene (also known as Cold-Induced Autoinflammatory Syndrome-1 [CIAS1]). CAPS disorders are inherited in an autosomal dominant pattern with male and female offspring equally affected. Features common to all disorders include fever, urticaria-like rash, arthralgia, myalgia, fatigue, and conjunctivitis.

In most cases, inflammation in CAPS is associated with mutations in the NLRP-3 gene, which encodes the protein cryopyrin, an important component of the inflammasome. Cryopyrin regulates the protease caspase-1 and controls the activation of interleukin-1 beta (IL-1β). Mutations in NLRP-3 result in an overactive inflammasome, resulting in excessive release of activated IL-1β that drives inflammation.

DIRA is an autoinflammatory, autosomal recessive disorder caused by loss of function mutations in the IL1RN gene, which encodes IL-1 receptor antagonist (IL-1ra), resulting in unopposed signaling of the proinflammatory cytokines IL-1α and IL-1β through the IL-1 receptor.

Interleukin-1 (IL-1) is a key cytokine that mediates the pathophysiology of many inflammatory processes, and it has been implicated as a causative factor in pericarditis. IL-1α and IL-1β bind to the universally expressed cell surface receptor, IL-1 Receptor type-1, triggering a cascade of inflammatory mediators. Pre-formed IL-1α is released by damaged/inflamed pericardial cells and may contribute to the maintenance and amplification of inflammation via activation of the NLRP3 inflammasome, which then augments the inflammatory response by production of IL-1β in a cascade amplification system.

12.2 Pharmacodynamics

C-Reactive Protein (CRP) and Serum Amyloid A (SAA) are indicators of inflammatory disease activity that are elevated in patients with CAPS. Elevated SAA has been associated with the development of systemic amyloidosis in patients with CAPS. Compared to placebo, treatment with ARCALYST resulted in sustained reductions from baseline in mean serum CRP and SAA to normal levels during the clinical trial. ARCALYST also normalized mean SAA from elevated levels.

CRP is also an indicator of inflammation in DIRA. Maintenance of CRP reduction was observed in a clinical trial of pediatric patients with DIRA [see Clinical Studies (14.2)].

CRP is also a recognized indicator of inflammation in pericarditis. Treatment with rilonacept was observed in a clinical trial with RP to be associated with resolution of acute pericarditis episodes, including rapid and sustained reduction in CRP, with a median time to normalization of 7 days [see Clinical Studies (14.3)].

12.3 Pharmacokinetics

The average trough levels of rilonacept were approximately 24 mcg/mL at steady state following weekly subcutaneous doses of 160 mg for up to 48 weeks in patients with CAPS. The steady state appeared to be reached by 6 weeks.

The average trough levels of rilonacept were approximately 23 mcg/mL at steady state, and the circulation half-life in vivo was approximately 7 days following a 320 mg loading dose and weekly subcutaneous doses of 160 mg for up to 36 weeks in patients with RP. Steady state appeared to be reached by approximately 2 weeks. No pharmacokinetic data are available in patients with hepatic or renal impairment.

No specific study was conducted to evaluate the effect of age, gender, or body weight on rilonacept exposure. Based on limited data obtained from the Phase 3 study RHAPSODY, steady state trough concentrations were similar between male and female patients. Age (26 to78 years) and body weight (50 to120 kg) did not appear to have a meaningful effect on trough rilonacept concentrations. The effect of race has not been assessed because of low numbers of non-Caucasian patients in the CAPS and RP programs, reflecting the epidemiology of these diseases.

In pediatric patients with DIRA (3 to 6 years of age and body weight 12.7 to 19.9 kg) who received weekly subcutaneous doses of 4.4 mg/kg of ARCALYST, the average steady-state trough levels ranged from 63.5 to 74.0 mg/mL during the period of 6 to 24 months from the start of treatment with ARCALYST.

13 NONCLINICAL TOXICOLOGY

13.1 Carcinogenesis, Mutagenesis, Impairment of Fertility

Long-term animal studies have not been performed to evaluate the carcinogenic potential of rilonacept.

A murine analog of rilonacept had no effects on fertility and reproductive performance in male and female mice at subcutaneous doses up to 200 mg/kg three times per week.

14 CLINICAL STUDIES

14.1 Cryopyrin-Associated Periodic Syndromes, Familial Cold Autoinflammatory Syndrome and Muckle-Wells Syndrome

The safety and efficacy of ARCALYST for the treatment of CAPS was demonstrated in a randomized, double-blind, placebo-controlled study (NCT00288704) with two parts (A and B) conducted sequentially in the same patients with FCAS and MWS.

Part A was a 6-week, randomized, double-blind, parallel-group period comparing ARCALYST at a dose of 160 mg weekly after an initial loading dose of 320 mg to placebo. Part B followed immediately after Part A and consisted of a 9-week, patient-blind period during which all patients received ARCALYST 160 mg weekly, followed by a 9-week, double-blind, randomized withdrawal period in which patients were randomly assigned to either remain on ARCALYST 160 mg weekly or to receive placebo. Patients were then given the option to enroll in a 24-week, open-label treatment extension phase in which all patients were treated with ARCALYST 160 mg weekly.

Using a daily diary questionnaire, patients rated the following five signs and symptoms of CAPS: joint pain, rash, feeling of fever/chills, eye redness/pain, and fatigue, each on a scale of 0 (none, no severity) to 10 (very severe). The study evaluated the mean symptom score using the change from baseline to the end of treatment.

The changes in mean symptom scores for the randomized parallel-group period (Part A) and the randomized withdrawal period (Part B) of the study are shown in Table 2. ARCALYST-treated patients had a larger reduction in the mean symptom score in Part A compared to placebo-treated patients. In Part B, mean symptom scores increased more in patients withdrawn to placebo compared to patients who remained on ARCALYST.

Table 2: Mean Symptom Scores
Part A | Placebo (n=24) | ARCALYST (n=23) | Part B | Placebo (n=23) | ARCALYST (n=22)
Pre-treatment Baseline Period (Weeks -3 to 0) | 2.4 | 3.1 | Active ARCALYST Baseline Period (Weeks 13 to 15) | 0.2 | 0.3
Endpoint Period (Weeks 4 to 6) | 2.1 | 0.5 | Endpoint Period (Weeks 22 to 24) | 1.2 | 0.4
LS [Differences are adjusted using an analysis of covariance model with terms for treatment and Part A baseline.] Mean Change from Baseline to Endpoint | -0.5 | -2.4 | LS Mean Change from Baseline to Endpoint | 0.9 | 0.1
95% confidence interval for difference between treatment groups | (-2.4, -1.3) [A confidence interval lying entirely below zero indicates a statistical difference favoring ARCALYST versus placebo.] |  | 95% confidence interval for difference between treatment groups | (-1.3, -0.4)

Daily mean symptom scores over time for Part A are shown in Figure 1.

Figure 1: Group Mean Daily Symptom Scores by Treatment Group in Part A and Single-blind ARCALYST Treatment Phase from Week -3 to Week 15

Improvement in symptom scores was noted within several days of initiation of ARCALYST therapy in most patients.

In Part A, patients treated with ARCALYST experienced more improvement in each of the five components of the composite endpoint (joint pain, rash, feeling of fever/chills, eye redness/pain, and fatigue) than placebo-treated patients.

In Part A, a higher proportion of patients in the ARCALYST group experienced improvement from baseline in the composite score by at least 30% (96% vs. 29% of patients), by at least 50% (87% vs. 8%) and by at least 75% (70% vs. 0%) compared to the placebo group.

Serum Amyloid A (SAA) and C-Reactive Protein (CRP) levels are acute phase reactants that are typically elevated in patients with CAPS with active disease. During Part A, mean levels of CRP decreased versus baseline for the ARCALYST treated patients, while there was no change for those on placebo (Table 3). ARCALYST also led to a decrease in SAA versus baseline to levels within the normal range.

Table 3. Mean Serum Amyloid A and C-Reactive Protein Levels Over Time in Part A
Part A | ARCALYST | Placebo
SAA (normal range: 0.7 – 6.4 mg/L) | (n=22) | (n=24)
Pre-treatment Baseline | 60 | 110
Week 6 | 4 | 110
CRP (normal range: 0.0 – 8.4 mg/L) | (n= 21) | (n=24)
Pre-treatment Baseline | 22 | 30
Week 6 | 2 | 28

During the open-label extension, reductions in mean symptom scores, serum CRP, and serum SAA levels were maintained for up to one year.

14.2 Deficiency of IL-1 Receptor Antagonist

The safety and efficacy of ARCALYST for the maintenance of remission of DIRA were demonstrated in a 2-year, open-label study (NCT01801449) of 6 pediatric patients who previously experienced clinical benefit from daily injections of an IL-1 receptor antagonist, anakinra. The study population included patients with a loss-of-function IL1RN mutations. Patients had a median age at baseline of 4.8 years (range 3.3 to 6.2), and stopped anakinra treatment 24 hours before initiation of ARCALYST.

Remission was defined using the following criteria: diary score of < 0.5 (reflecting no fever, skin rash and bone pain), acute phase reactants (<0.5 mg/dL CRP), absence of objective skin rash, and no radiological evidence of active bone lesions.

Following an ARCALYST loading dose of 4.4 mg/kg subcutaneously, patients received a once-weekly maintenance dose of 2.2 mg/kg (up to a maximum 160 mg), and were assessed for remission and possible dose escalation. During the first 3 months of ARCALYST administration at the 2.2 mg/kg dose, five of 6 patients exhibited recurrence of pustular rash and therefore the dose was escalated to 4.4 mg/kg once weekly (up to a maximum of 320 mg). One patient remained on the 2.2 mg/kg once-weekly dose.

All patients met the primary endpoint of the study, remission at 6 months and sustained the remission for the remainder of the 2-year study. No patient required steroid use during the study.

14.3 Recurrent Pericarditis

The efficacy and safety of ARCALYST were evaluated in the Phase 3 study RHAPSODY (NCT03737110), a double-blind, placebo-controlled, randomized withdrawal, multinational study. The study consisted of a 12-week run-in followed by a double-blind, placebo-controlled, randomized withdrawal period.

In the run-in period, adult patients received a loading dose of ARCALYST 320 mg followed by 160 mg weekly. Patients between 12 and 17 years of age received a loading dose of ARCALYST 4.4 mg/kg (up to 320 mg) followed by 2.2 mg/kg (up to 160 mg) weekly. During the run-in period, patients tapered and discontinued standard-of-care therapies.

In the withdrawal period, patients were randomized 1:1 to remain on ARCALYST 160 mg weekly or to receive placebo. The randomized withdrawal period continued until the pre-specified number of primary efficacy endpoint events (pericarditis recurrence) had accrued.

Patients recorded scores for pericarditis pain in a daily diary using the 0 to 10 NRS scale. Measurements of CRP, electrocardiograms, and echocardiograms were conducted at intervals during study visits and to assess pericarditis recurrence

Patients who experienced pericarditis recurrence were eligible for open-label ARCALYST (bailout).

A total of 86 patients (mean age 45 years [range 13-78], 57% females) with symptomatic pericarditis recurrence were enrolled and received study treatment. Of these, 73 (85%) had a diagnosis of "idiopathic" pericarditis, and the remainder post-cardiac injury pericarditis. The mean duration of disease was 2.4 years with a mean of 4.4 pericarditis events per year including the qualifying pericarditis event (0-10 point Numerical Rating Scale [NRS] ≥ 4 and CRP ≥ 1 mg/dL). Mean qualifying NRS pain score was 6.2, and mean qualifying CRP level was 6.2 mg/dL.

During the run-in period, daily NRS pain scores and CRP levels decreased as shown in Figure 2.

Figure 2: Summary of Pain NRS and CRP Means

Time to treatment response (NRS ≤ 2 and CRP ≤ 0.5 mg/dL) is shown in Table 4. The median time to treatment response was 5.0 days. All patients were required to taper off standard-of-care pericarditis medications before randomization, and median time to rilonacept monotherapy was 7.9 weeks during the run-in period.

Of the 86 patients enrolled, 41 (48%) were on treatment with corticosteroids (CS) at baseline (mean treatment duration of 20 weeks).

Table 4. Time to Treatment Response: Run-in Period
 | ARCALYST (N=86)
Subjects with baseline NRS score >2 or CRP > 0.5 mg/dL | 79
Subjects achieving treatment response | 77 (97%)
Days to treatment response (median; 95% CI) | 5 (4, 7)
Time to monotherapy (median; 95% CI) | 8 (7, 8) weeks

The primary efficacy endpoint was time to first adjudicated pericarditis recurrence (based on pain, CRP and clinical signs) in the event-driven withdrawal period. Of 61 patients randomized, 23 patients (74%) in the placebo arm had a recurrence compared with 2 patients (7%) in the rilonacept arm who temporarily discontinued treatment for 1 – 3 doses. The median time-to-recurrence on rilonacept could not be estimated because too few events occurred and was 8.6 weeks (95% CI 4.0, 11.7) on placebo with a hazard ratio of 0.04 (p < 0.0001); rilonacept reduced the risk of recurrence by 96% (Figure 3).

The two recurrence events in the rilonacept group happened in association with temporary interruptions of the trial-drug regimen, of one to three weekly doses. In the placebo group, all 23 patients who had pericarditis recurrence received bailout rilonacept, with resolution of the episodes.

Figure 3. Primary Efficacy Endpoint for RHAPSODY

Kaplan-Meier Curves for Time to Pericarditis Recurrence Based on ITT Analysis Set

Secondary efficacy endpoints were the proportion of patients with maintenance of clinical response, the percentage of trial days with none/minimal pericarditis pain (NRS ≤ 2) each measured at Week 16 of the withdrawal period. Results are summarized in Table 5.

Table 5. Secondary Efficacy Endpoints for RHAPSODY
 | ARCALYST n=21 | Placebo n=20 | Increase (%) | p-value
Number of patients who maintained response at Week 16 | 17 | 4 | 61 | 0.0002
Percentage of days with NRS ≤2 | 92 | 40 | 52 | <0.0001

16 HOW SUPPLIED/STORAGE AND HANDLING

ARCALYST (rilonacept) for injection is supplied as a sterile, white to off-white, preservative-free, lyophilized powder in single-dose vials.

Each 220 mg vial of ARCALYST is supplied in a carton containing one vial (NDC 73604-914-01) or four vials (NDC 73604-914-04).

STORAGE AND HANDLING

Store refrigerated at 2°C to 8°C (36°F to 46°F) in the original carton to protect from light. Do not use beyond the date stamped on the label. After reconstitution, ARCALYST may be kept at room temperature, protected from light [see Dosage and Administration (2.5)].

17 PATIENT COUNSELING INFORMATION

Advise the patient to read the FDA-approved patient labeling (Patient Information and Instructions for Use).

Assessment of Patient's or Caregiver's Administration of ARCALYST: The first injection of ARCALYST should be performed under the supervision of a qualified healthcare professional. If a patient or caregiver is to administer ARCALYST, instruct them on aseptic reconstitution of the lyophilized product and injection technique. The ability to inject subcutaneously should be assessed to ensure proper administration of ARCALYST, including rotation of injection sites. (See Patient Information Leaflet for ARCALYST®). ARCALYST should be reconstituted with preservative-free Sterile Water for Injection to be provided by the pharmacy. If the total volume of dose needed is greater than 2 mL, provide instruction about how to divide the total dose and how to administer the 2 injections. Remind patients to discard vials with unused product. A sharps disposal container should be used for disposal of vials, needles and syringes. Instruct patients or caregivers in proper vial, syringe, and needle disposal, and they should be cautioned against reuse of these items [see Dosage and Administration (2.5)].

Injection-site Reactions: Explain to patients that almost half of the patients in the clinical trials experienced a reaction at the injection site. Injection-site reactions may include pain, erythema, swelling, pruritus, bruising, mass, inflammation, dermatitis, edema, urticaria, vesicles, warmth, and hemorrhage. Caution patients to avoid injecting into an area that is already swollen or red. Any persistent reaction should be brought to the attention of the prescribing physician [see Adverse Reactions (6.1)].

Infections: Caution patients that ARCALYST has been associated with serious, life-threatening infections, and not to initiate treatment with ARCALYST if they have a chronic or active infection. Advise patients to contact their healthcare professional immediately if they develop an infection after starting ARCALYST. Treatment with ARCALYST should be discontinued if a patient develops a serious infection. Advise patients not to take any IL-1 blocking drug, including ARCALYST, if they are also taking a drug that blocks TNF such as etanercept, infliximab, or adalimumab. Use of ARCALYST with other IL-1 blocking agents, such as anakinra, is not recommended [see Warnings and Precautions (5.1)].

Vaccinations: Prior to initiation of therapy with ARCALYST, review the vaccination history with adult and pediatric patients, parent(s), and/or caregiver relative to current medical guidelines for vaccine use, including taking into account the potential of increased risk of infection during treatment with ARCALYST [see Warnings and Precautions (5.5)].

Manufactured by:

Kiniksa Pharmaceuticals (UK), Ltd.
London, UK W1J 7NJ
U.S. License Number 2236

1-833-KINIKSA (1-833-546-4572)
NDC 73604-914-04 and NDC 73604-914-01

ARCALYST® is a registered trademark of Regeneron Pharmaceuticals, Inc.
© 2025 Kiniksa Pharmaceuticals (UK), Ltd.

All rights reserved.

Patient Information
ARCALYST® (ARK-a-list)
(rilonacept)
For Injection
For Subcutaneous Use

Read this Patient Information before you or your child start taking ARCALYST and each time you or your child get a refill. There may be new information. This Patient Information leaflet does not take the place of talking with the healthcare provider about your or your child's medical condition or treatment.

What is ARCALYST?

- ARCALYST is a prescription medicine called an interleukin-1 (IL-1) blocker.
- ARCALYST is used to treat adults and children 12 years and older with Cryopyrin-Associated Periodic Syndromes (CAPS), including Familial Cold Autoinflammatory Syndrome (FCAS), and Muckle-Wells Syndrome (MWS).
- ARCALYST is used to maintain control of symptoms of Deficiency of Interleukin-1 Receptor Antagonist (DIRA) in adults and children weighing at least 22 pounds (10 kg).
- ARCALYST is used to treat Recurrent Pericarditis (RP) and reduce the risk of recurrence in adults and children 12 years and older.

It is not known if ARCALYST is safe and effective in children under 12 years of age.
It is not known if ARCALYST is safe and effective in children with DIRA weighing less than 22 pounds (10 kg).

What is the most important information I should know about ARCALYST?
ARCALYST can affect your or your child's immune system. ARCALYST can lower the ability of your or your child's immune system to fight infections. Serious infections, including life-threatening infections and death, have happened in people taking ARCALYST. Taking ARCALYST can make you or your child more likely to get infections, including life-threatening serious infections, or may make any infection that you or your child have worse.
You or your child should not begin treatment with ARCALYST if you or your child have an infection or have infections that keep coming back (chronic infection).
After starting ARCALYST, if you or your child get an infection, any sign of an infection, including a fever, cough, flu-like symptoms, or have any open sores on your body, call the healthcare provider right away. Treatment with ARCALYST should be stopped if you or your child get a serious infection.
You or your child should not take medicines that block tumor necrosis factor (TNF), such as Enbrel® (etanercept), Humira® (adalimumab), or Remicade® (infliximab), while you or your child are taking ARCALYST. You or your child should also not take other medicines that block interleukin-1 (IL-1), such as Kineret® (anakinra), while taking ARCALYST. Taking ARCALYST with any of these medicines may increase your or your child's risk of getting a serious infection.
Before starting treatment with ARCALYST, tell the healthcare provider if you or your child:

- think you have an infection.
- are being treated for an infection.
- have signs of an infection, such as fever, cough, or flu-like symptoms.
- have any open sores on your body.
- have a history of infections that keep coming back.
- have asthma. People with asthma may have an increased risk of infection.
- have diabetes or an immune system problem. People with these problems have a higher chance for infections.
- have tuberculosis (TB), or if you have been in close contact with someone who has had tuberculosis.
- have or have had HIV, hepatitis B, or hepatitis C.
- take other medicines that affect your immune system.

Before you or your child begin treatment with ARCALYST, talk with the healthcare provider about your or your child's vaccine history. Ask the healthcare provider whether you or your child should receive any vaccines, including the pneumonia vaccine and flu vaccine, before you or your child begin treatment with ARCALYST.

What should I tell my or my child's healthcare provider before taking ARCALYST?
ARCALYST may not be right for you or your child. Before taking ARCALYST, tell your or your child's healthcare provider about all medical conditions, including if you or your child:

- are scheduled to receive any vaccines. You or your child should not receive live vaccines if you take ARCALYST. See "What is the most important information I should know about ARCALYST?"
- are pregnant or plan to become pregnant. It is not known if ARCALYST will harm your unborn child. Tell the healthcare provider right away if you become pregnant while taking ARCALYST.
- are breastfeeding or plan to breastfeed. It is not known if ARCALYST passes into breast milk. Talk to the healthcare provider about the best way to feed your child during treatment with ARCALYST.

Tell the healthcare provider about all the medicines you or your child take, including prescription and over-the-counter medicines, vitamins, and herbal supplements.
Especially tell the healthcare provider if you or your child take other medicines that affect the immune system, such as:

- See "What is the most important information I should know about ARCALYST?"
- Corticosteroids

Know the medicines you or your child take. Keep a list of the medicines and show it to your or your child's healthcare provider and pharmacist every time you or your child get a new prescription.
If you have any questions about any of this information, ask the healthcare provider.

How should I take ARCALYST?
See the Instructions for Use at the end of this Patient Information leaflet.

- Take or give ARCALYST exactly as prescribed by the healthcare provider.
- ARCALYST is given by injection under the skin (subcutaneous injection) 1 time each week.
- ARCALYST should not be given more than 1 time each week.
- The healthcare provider will tell you how much ARCALYST to take or give your child, and show you how to prepare and give the injection.
- Do not try to give ARCALYST injections until you are sure that you understand how to prepare and inject your dose. Call the healthcare provider or pharmacist if you have any questions, or if you would like more training.
- If you or your child take too much ARCALYST, call the healthcare provider or go to the nearest hospital emergency room right away.

What are the possible side effects of ARCALYST?
ARCALYST can cause serious side effects, including:

- See "What is the most important information I should know about ARCALYST?"
- Risk of Cancer. Medicines that affect the immune system may increase the risk of getting cancer.
- Allergic Reaction. Stop taking or giving ARCALYST and call the healthcare provider or get emergency care right away if you or your child get any of the following symptoms of an allergic reaction while taking ARCALYST:

- rash

- swollen face

- trouble breathing

- Changes in your blood cholesterol and triglycerides (lipids). Your or your child's healthcare provider will do blood tests to check for these changes.

In people with CAPS and RP, the most common side effects of ARCALYST include:

- Injection-site reactions including: pain, redness, swelling, itching, bruising, lumps, inflammation, skin rash, blisters, warmth, and bleeding at the injection site.
- Upper respiratory tract infections
- Joint and muscle aches in RP

In people with DIRA, the most common side effects of ARCALYST include:

- Upper respiratory infection
- Rash
- Ear infection
- Sore throat
- Runny nose

These are not all the possible side effects of ARCALYST. Tell your or your child's healthcare provider if you or your child have any side effects that bother you or do not go away. For more information, ask your or your child's healthcare provider or pharmacist. Call your or your child's healthcare provider for medical advice about side effects. You may report side effects to FDA at 1-800-FDA-1088.

How should I store ARCALYST?

- Keep ARCALYST in the carton it comes in to protect from light.
- Store ARCALYST in the refrigerator from 36°F to 46°F (2°C to 8°C). Call your pharmacy if you have any questions.
- Refrigerated ARCALYST can be used until the expiration date printed on the vial and carton.
- ARCALYST may be kept at room temperature after mixing with Sterile Water for Injection, USP, and should be used within 3 hours of mixing. Keep ARCALYST away from light.

Keep ARCALYST, injection supplies, and all other medicines out of the reach of children.

General Information about the safe and effective use of ARCALYST.
Medicines are sometimes prescribed for purposes other than those listed in a Patient Information leaflet. Do not use ARCALYST for a condition for which it was not prescribed. Do not give ARCALYST to other people even if they have the same symptoms that you have. It may harm them.
You can ask your healthcare provider or pharmacist for information about ARCALYST that is written for health professionals.

What are the ingredients in ARCALYST?
Active ingredient: rilonacept.
Inactive ingredients: glycine, histidine, L-arginine, polyethylene glycol 3350 and sucrose.
Manufactured by: Kiniksa Pharmaceuticals (UK), Ltd., London, UK W1J 7NJ
U.S. License No. 2236
ARCALYST is a registered trademark of Regeneron Pharmaceuticals, Inc. All other trademarks are the property of their respective owners.
© 2025 Kiniksa Pharmaceuticals (UK), Ltd. All rights reserved.
For more information about ARCALYST, call 1-833-KINIKSA (1-833-546-4572), or visit www.ARCALYST.com.

This Patient Information has been approved by the U.S. Food and Drug Administration.
Revised: October 2025

Instructions for Use

ARCALYST® (ARK-a-list)
(rilonacept)
For Injection
For Subcutaneous Use

It is important that you read, understand, and follow these instructions before you or your child start using ARCALYST so that you prepare and inject the medicine the right way.

Do not try to inject ARCALYST until you have been shown the right way to give the injections by your or your child's healthcare provider.

How do I prepare and give an ARCALYST injection?

Step 1: Setting up for an injection

1. Choose a table or other flat area to set up the supplies for your injection. Be sure the area is clean or clean it with an antiseptic or soap and water.
2. Wash your hands well with soap and water about 20 seconds, and dry with a clean towel.
3. Put the following supplies on the cleaned area for each injection (see Figure A):

Figure A

Supplies needed to give your ARCALYST injection:

- 1 vial of ARCALYST (powder for mixing)

Additional supplies needed (available from the pharmacy):

- 1 vial of preservative-free Sterile Water for Injection, USP
- 2 sterile, 3-milliliter (mL) disposable syringes with markings at each 0.1 mL (see Figure B):
  - 1 syringe for mixing ARCALYST
  - 1 syringe for injection
    Figure B
- 2 sterile disposable needles (18-gauge, 1-inch or 1½-inch) and 1 sterile disposable needle (26-gauge, ½-inch) with needle covers
  - 1 18-gauge needle for transferring the Sterile Water for Injection, USP, to the ARCALYST vial
  - 1 18-gauge needle for withdrawing the mixed solution
  - 1 26-gauge needle for injection
- 4 alcohol wipes
- 1 gauze pad
- 1 sharps disposal container for throwing away (disposing of) used needles, syringes, and vials

Note:

- Do not use Sterile Water for Injection, USP, syringes or needles other than those provided by your pharmacy. Contact your pharmacy if you need replacement syringes or needles.
- Do not touch the needles or the rubber stoppers on the vials with your hands. If you touch the rubber stopper, clean it with a new alcohol wipe.
- If you touch a needle or the needle touches any surface, throw away the entire syringe in the sharps disposal container and use a new syringe.
- Do not reuse needles or syringes.
- To protect yourself and others from possible needlesticks, it is very important to throw away each syringe, with the needle attached, in the sharps disposal container right after use.

Step 2: Preparing the vials

1. Check the expiration date on the carton or on the vial of ARCALYST. Do not use the vial if the expiration date has passed. Contact your pharmacy if the expiration date has passed.
2. Check the expiration date on the vial of Sterile Water for Injection, USP. Do not use the vial if the expiration date has passed. Contact your pharmacy for assistance.
3. Remove the protective plastic caps from both vials.
4. Clean the top of each vial with an alcohol wipe. Use 1 wipe for each vial and wipe in 1 direction around the top of the vial (see Figure C).
  Figure C
5. Check the expiration date on the needle. Do not use the needle if the expiration date has passed. Contact your pharmacy if the expiration date has passed.
6. Open the wrapper that contains 1 of the 18-gauge needles by pulling apart the tabs and set it aside for later use. Do not remove the needle cover. This needle will be used to mix the water with ARCALYST powder in the vial.
7. Check the expiration date on the syringe. Do not use the syringe if the expiration date has passed. Contact your pharmacy if the expiration date has passed.
8. Open the wrapper that contains the syringe by pulling apart the tabs (see Figure D).
9. Hold the barrel of the syringe with one hand and use your other hand to twist the 18-gauge needle with the cover onto the tip of the syringe until it fits firmly (see Figure E).
  Figure D
  Figure E
10. Hold the syringe upright at eye level. With the needle cover still on the 18-gauge needle, pull back the plunger to the 2.3 mL mark to fill the syringe with air (see Figure F).
  Figure F
11. Hold the syringe in one hand and use the other hand to pull the needle cover straight off. Do not twist the needle as you pull off the cover. Place the needle cover aside. Hold the syringe in the hand that you will use to mix your medicine. Hold the Sterile Water for Injection, USP, vial on a firm surface with your other hand. Slowly insert the needle straight through the rubber stopper. Do not bend the needle. Push the plunger in all the way to push the air into the vial (see Figure G).
  Figure G
12. Hold the vial in one hand and the syringe in the other hand and carefully turn the vial upside down so that the needle is pointing straight up (see Figure H).
13. Make sure the tip of the needle is covered by the liquid and slowly pull back on the plunger to the 2.3 mL mark to withdraw the Sterile Water for Injection, USP, from the vial (see Figure H).
  Figure H
14. Keep the vial upside down and gently tap the syringe with your fingers until any air bubbles rise to the top of the syringe.
15. To remove the air bubbles, gently push in the plunger so only the air is pushed out of the syringe and back into the bottle.
16. After removing the air bubbles, check the syringe to be sure that the right amount of Sterile Water for Injection, USP, has been drawn into the syringe (see Figure I).
  Figure I
17. Carefully remove the syringe with the 18-gauge needle from the Sterile Water for Injection, USP, vial. Do not touch the needle.

Step 3: Mixing ARCALYST

18. With one hand, hold the ARCALYST vial on a firm surface.
19. With the other hand, take the syringe with the 18-gauge needle that contains the Sterile Water for Injection, USP, and slowly insert the needle straight down through the rubber stopper of the ARCALYST vial.
20. Gently push the plunger in all the way to inject the Sterile Water for Injection, USP, into the vial, aiming the stream of Sterile Water for Injection, USP, down the side of the vial into the powder (see Figure J).
  Figure J
21. Remove the syringe and needle from the rubber stopper and throw away the needle, syringe, and Sterile Water for Injection, USP, vial in the sharps disposal container. Do not try to put the needle cover back on the needle (see Figure K).
  Figure K
22. Hold the vial containing the ARCALYST and Sterile Water for Injection, USP, sideways (not upright) as shown (see Figure L). Do not touch the rubber stopper. Quickly shake the vial back and forth (side-to-side) for about 1 minute.
  Figure L
23. Put the vial back on the table and let the vial sit for about 1 minute.
24. Check the vial for any particles or clumps of powder that have not dissolved.
25. If the powder has not completely dissolved, shake the vial quickly back and forth for 30 seconds more. Let the vial sit for about 1 minute.
26. Repeat Step 25 until the powder is completely dissolved and the solution is clear (see Figure M).
  Figure M
27. The mixed ARCALYST should be thick, clear, and colorless to pale yellow. Do not use the mixed liquid if it is discolored or cloudy, or if particles are in it.
  Note: Contact your pharmacy to report any mixed ARCALYST that is discolored, cloudy or contains particles.
28. ARCALYST may be kept at room temperature after mixing. ARCALYST should be used within 3 hours of mixing. Keep ARCALYST away from light.

Step 4: Preparing the Injection

29. Hold the ARCALYST vial in one hand and wipe in 1 direction around the top of the ARCALYST vial with a new alcohol wipe with the other hand (see Figure N).
  Figure N
30. Take a new sterile, disposable 18-gauge needle and attach it firmly to a new syringe without removing the needle cover (see Figures O and P).
  Figure O
  Figure P
31. To draw air into the syringe, hold the syringe upright at eye level. Do not remove the needle cover. Pull back the plunger on the syringe to the mark that is equal to the amount of mixed ARCALYST that the healthcare provider has prescribed for you to inject (see Figure Q).
  Figure Q
32. Hold the syringe in one hand and use the other hand to pull the needle cover straight off. Do not twist the needle as you pull off the cover. Place the needle cover aside and be careful not to touch the needle. Keep the ARCALYST vial on a flat firm surface and slowly insert the needle straight down through the rubber stopper. Push the plunger down and inject all of the air into the vial (see Figure R).
  Figure R
33. Hold the vial in one hand and the syringe in the other hand and carefully turn the vial upside down so that the needle is pointing straight up. Hold the vial at eye level.
34. Keep the tip of the needle in the liquid and slowly pull back on the plunger to the mark on the syringe that matches the amount of medicine prescribed by your or your child's healthcare provider (see Figure S).
  Figure S
  Note: The maximum amount of medicine that you can withdraw from 1 vial of ARCALYST is 2 mL. If the amount of medicine you need to withdraw for your or your child's dose of ARCALYST is more than 2 mL, you will need to use 2 vials. The healthcare provider will tell you the right amount of medicine to withdraw from the 2 vials and how to give the 2 injections. Always use new syringes and needles for each injection.
35. Keep the vial upside down with the needle straight up, and gently tap the syringe until any air bubbles rise to the top of the syringe (see Figure T).
  It is important to remove air bubbles so that you withdraw the right amount of medicine from the vial.
  Figure T
36. To remove the air bubbles, slowly and gently push in the plunger so only the air is pushed through the needle.
37. Check to make sure that you have the amount of medicine prescribed by the healthcare provider in the syringe. Remove the syringe with the needle from the vial.
38. You will now prepare to switch needles.
39. To remove the 18-gauge needle and replace it with the new 26-gauge needle for injection, place the syringe with the 18-gauge needle and the needle cap on a flat surface. Use one hand to slide the 18-gauge needle into the needle cap and scoop upwards to cover the needle (see Figure U1).
40. When the needle is covered, push the needle cap toward the syringe to fully attach it with one hand to prevent an accidental stick with the needle (see Figure U2). Twist off and remove the 18-gauge needle with the needle cap (see Figures U3 and U4).
  Figure U
41. Open a new sterile, disposable 26-gauge needle (see Figure V) and attach securely to the syringe without removing the needle cover (see Figure W).
  Figure V
  Figure W
42. Throw away the ARCALYST vial and 18-gauge needle that still has the needle cover attached to it in the sharps disposal container even if there is medicine left in the vial (see Figure X). Do not use any vial of ARCALYST more than 1 time.
  Figure X

Step 5: Giving the Injection

43. ARCALYST is given by injection into the tissue directly under the skin (subcutaneous injection). Do not inject ARCALYST into any muscle, vein, or artery.
  You should change (rotate) the injection site each time you inject ARCALYST.
  If you need to use 2 vials and give 2 injections for your or your child's prescribed dose of ARCALYST, you should use 2 different injection sites.
  Changing injection sites helps to prevent irritation and allows the medicine to be completely absorbed. Ask your or your child's healthcare provider if you have any questions about changing injection sites.
  - Do not inject into skin that is tender, red, or hard. If an area is tender or feels hardened, choose another site for injection until the tenderness or hardening goes away.
  - Tell your or your child's healthcare provider about any skin reactions including redness, swelling, or hardening of the skin.
  - Areas where you may inject ARCALYST include the left and right sides of the abdomen, and the left and right thighs. If you are giving the injection to your child or someone else, the upper left and right arms may also be used for injection (see Figure Y):
  Do not inject within a 2-inch area around the belly button.
  Figure Y
44. Choose the area for the injection. Clean the area in a circular motion with a new alcohol wipe. Begin at the center of the injection site and move outward. Let the alcohol air dry completely.
45. Remove the needle cover and hold the syringe in one hand like you would hold a pencil.
46. With the other hand, gently pinch a fold of skin at the cleaned injection site (see Figure Z).
  Figure Z
47. Use a quick "dart like" motion to insert the needle straight into the skin at a 90-degree angle (see Figure AA). Do not push down on the plunger while inserting the needle into the skin.
  For small children or people with little fat under the skin, you may need to hold the syringe and needle at a 45-degree angle (see Figure BB).
  Figure AA
  Figure BB
48. After the needle is completely in the skin, let go of the pinched skin.
49. With your free hand, hold the syringe near the bottom. Gently pull back the plunger. If blood comes into the syringe, the needle has entered a blood vessel. Remove the needle and throw away (discard) the syringe and needle in the sharps disposal container. Start over with "Step 1: Setting up for an injection" using new supplies (syringes, needles, alcohol swabs, gauze pad, and new vials of ARCALYST and Sterile Water for Injection, USP).
50. If no blood comes into the syringe, inject all the medicine in the syringe at a slow, steady rate, pushing the plunger all the way down. It may take up to 30 seconds to inject the entire dose.
51. Pull the needle out of the skin and hold a gauze pad over the injection site for several seconds (see Figure CC).
  Figure CC
52. Do not replace the needle cover. Throw away the vials, used syringes and needles in an FDA-cleared sharps disposal container (see Figure DD). Do not throw away vials, needles, or syringes in the household trash or recycle.
  If you do not have an FDA-cleared sharps disposal container, you may use a household container that is:
  - made of a heavy-duty plastic,
  - can be closed with a tight-fitting, puncture-resistant lid, without sharps being able to come out,
  - upright and stable during use,
  - leak-resistant, and
  - properly labeled to warn of hazardous waste inside the container.
  Figure DD
  When your sharps disposal container is almost full, you will need to follow your community guidelines for the right way to dispose of your sharps disposal container. There may be state or local laws about how you should throw away used needles and syringes. For more information about safe sharps disposal, and for specific information about sharps disposal in the state that you live in, go to the FDA's website at: http://www.fda.gov/safesharpsdisposal
  - Do not reuse or share your syringes with other people.
  - Do not dispose of your used sharps disposal container in your household trash unless your community guidelines permit this.
  - Do not recycle your used sharps disposal container.
53. Keep the sharps disposal container out of the reach of children.
54. Used alcohol wipes can be thrown away in the household trash.

Contact your or your child's healthcare provider right away with any questions or concerns about ARCALYST.

Manufactured by:

Kiniksa Pharmaceuticals (UK), Ltd., London, UK W1J 7NJ

U.S. License Number 2236

ARCALYST is a registered trademark of Regeneron Pharmaceuticals, Inc.

© 2025 Kiniksa Pharmaceuticals (UK), Ltd. All rights reserved.

For more information about ARCALYST, call 1-833-KINIKSA (1-833-546-4572), or visit www.ARCALYST.com.

This Instructions for Use has been approved by the U.S. Food and Drug Administration.

Revised: October 2025

PRINCIPAL DISPLAY PANEL - 220 mg Vial Carton - NDC 73604-914-04

NDC 73604-914-04

Arcalyst®
(rilonacept)
For Injection

220 mg per vial

For subcutaneous use only
Must be reconstituted
Store refrigerated at 2°C to 8°C (36°F to 46°F) until use.
Protect from light.

Rx ONLY
KINIKSA
Contents: four (4) single-dose vials

PRINCIPAL DISPLAY PANEL - 220 mg Vial Carton - NDC 73604-914-01

NDC 73604-914-01

Arcalyst®
(rilonacept)
For Injection

220 mg per vial

For subcutaneous use only.
Must be reconstituted.
Store refrigerated at 2°C to 8°C (36°F to 46°F) until use.
Protect from light.

Rx ONLY
KINIKSA
Contents: one single-dose vial